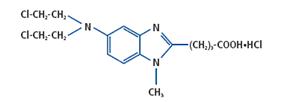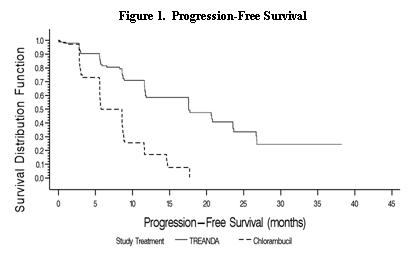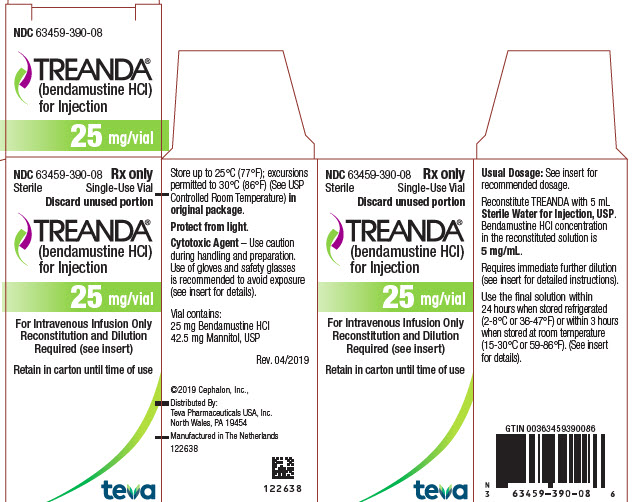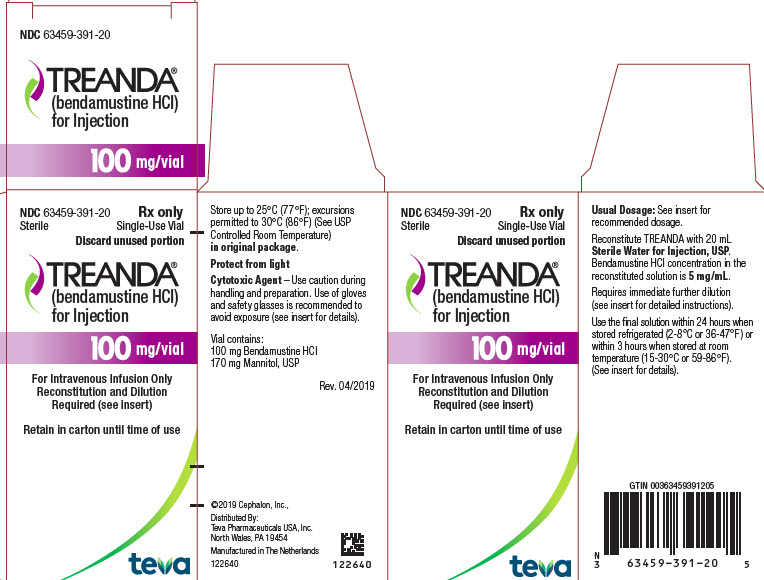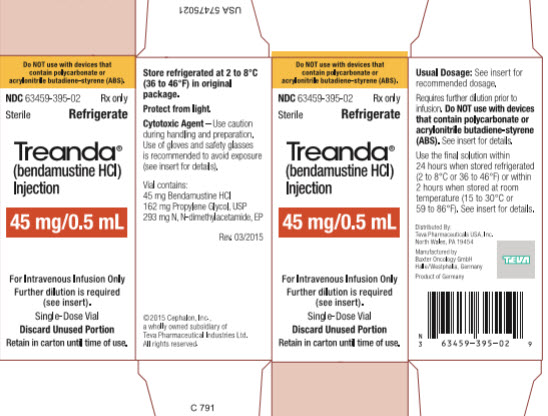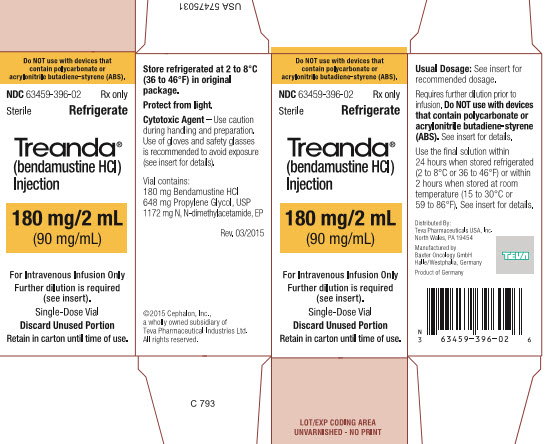 DRUG LABEL: TREANDA
NDC: 63459-395 | Form: INJECTION, SOLUTION, CONCENTRATE
Manufacturer: Cephalon, LLC
Category: prescription | Type: HUMAN PRESCRIPTION DRUG LABEL
Date: 20221027

ACTIVE INGREDIENTS: BENDAMUSTINE HYDROCHLORIDE 45 mg/0.5 mL
INACTIVE INGREDIENTS: PROPYLENE GLYCOL; N,N-DIMETHYLACETAMIDE

HIGHLIGHTS OF PRESCRIBING INFORMATION

These highlights do not include all the information needed to use TREANDA safely and effectively. See full prescribing information for TREANDA.
TREANDA® (bendamustine hydrochloride) injection, for intravenous use
TREANDA® (bendamustine hydrochloride) for injection, for intravenous use
Initial U.S. Approval: 2008

1 INDICATIONS AND USAGE

TREANDA is an alkylating drug indicated for treatment of patients with:

- Chronic lymphocytic leukemia (CLL). Efficacy relative to first line therapies other than chlorambucil has not been established. (1.1)
- Indolent B-cell non-Hodgkin lymphoma (NHL) that has progressed during or within six months of treatment with rituximab or a rituximab-containing regimen. (1.2)

2 DOSAGE AND ADMINISTRATION

TREANDA is available in two formulations, a solution (TREANDA Injection) and a lyophilized powder (TREANDA for Injection). (2.1)
Do not use TREANDA injection with devices that contain polycarbonate or acrylonitrile-butadiene-styrene (ABS), including most Closed System Transfer Devices (CSTDs). (2.1, 2.4)
For CLL:

- 100 mg/m^2 infused intravenously over 30 minutes on Days 1 and 2 of a 28-day cycle, up to 6 cycles (2.2)

For NHL:

- 120 mg/m^2 infused intravenously over 60 minutes on Days 1 and 2 of a 21-day cycle, up to 8 cycles (2.3)

3 DOSAGE FORMS AND STRENGTHS

Injection: 45 mg/0.5 mL or 180 mg/2 mL (90 mg/mL) in a single-dose vial. (3)
For Injection: 25 mg or 100 mg lyophilized powder in a single-dose vial for reconstitution. (3)

4 CONTRAINDICATIONS

TREANDA is contraindicated in patients with a history of a hypersensitivity reaction to bendamustine. Reactions have included anaphylaxis and anaphylactoid reactions. (4, 5.4)

5 WARNINGS AND PRECAUTIONS

- Myelosuppression: Delay or reduce dose and restart treatment based on ANC and platelet count recovery. (5.1)
- Infections: Monitor for fever and other signs of infection or reactivation of infections and treat promptly. (5.2)
- Progressive multifocal leukoencephalopathy (PML): Monitor for new or worsening neurological, cognitive or behavioral signs or symptoms suggestive of PML. (5.3)
- Anaphylaxis and Infusion Reactions: Severe and anaphylactic reactions have occurred; monitor clinically and discontinue drug for severe reactions. Pre-medicate in subsequent cycles for milder reactions. (5.4)
- Tumor Lysis Syndrome: May lead to acute renal failure and death; anticipate and use supportive measures in patients at high risk. (5.5)
- Skin Reactions: Discontinue for severe skin reactions. Cases of SJS, DRESS and TEN, some fatal, have been reported. (5.6)
- Hepatotoxicity: Monitor liver chemistry tests prior to and during treatment. (5.7)
- Other Malignancies: Pre-malignant and malignant diseases have been reported. (5.8)
- Extravasation Injury: Take precautions to avoid extravasation, including monitoring intravenous infusion site during and after administration. (5.9)
- Embryo-Fetal Toxicity: Can cause fetal harm. Advise females of reproductive potential of the potential risk to a fetus and to use an effective method of contraception. (5.10, 8.1, 8.3)

6 ADVERSE REACTIONS

- Adverse reactions (frequency >5%) during infusion and within 24 hours post-infusion are nausea and fatigue. (6.1)
- Most common adverse reactions (≥15%) for CLL are anemia, thrombocytopenia, neutropenia, lymphopenia, leukopenia, pyrexia, nausea, vomiting. (6.1, 6.2)
- Most common adverse reactions (≥15%) for NHL are lymphopenia, leukopenia, anemia, neutropenia, thrombocytopenia, nausea, fatigue, vomiting, diarrhea, pyrexia, constipation, anorexia, cough, headache, weight decreased, dyspnea, rash, and stomatitis. (6.1, 6.2)

To report SUSPECTED ADVERSE REACTIONS, contact Teva Pharmaceuticals at 1-888-483-8279 or FDA at 1-800-FDA-1088 or www.fda.gov/medwatch.

7 DRUG INTERACTIONS

Consider alternative therapies that are not CYP1A2 inducers or inhibitors during treatment with TREANDA. (7)

8 USE IN SPECIFIC POPULATIONS

- Lactation: Advise not to breastfeed. (8.2)
- Infertility: May impair fertility. (8.3)
- Renal Impairment: Do not use in patients with creatinine clearance <30 mL/min. (8.6)
- Hepatic Impairment: Do not use in patients with total bilirubin 1.5-3 x ULN and AST or ALT 2.5-10 x ULN, or total bilirubin >3 x ULN. (8.7)

FULL PRESCRIBING INFORMATION

1 INDICATIONS AND USAGE

1.1 Chronic Lymphocytic Leukemia (CLL)

TREANDA® is indicated for the treatment of patients with chronic lymphocytic leukemia. Efficacy relative to first line therapies other than chlorambucil has not been established.

1.2 Non-Hodgkin Lymphoma (NHL)

TREANDA is indicated for the treatment of patients with indolent B-cell non-Hodgkin lymphoma that has progressed during or within six months of treatment with rituximab or a rituximab-containing regimen.

2 DOSAGE AND ADMINISTRATION

2.1 Selection of TREANDA Formulation to Administer

TREANDA is available in two formulations, a solution (TREANDA Injection) and a lyophilized powder (TREANDA for Injection).

Do not use TREANDA Injection if you intend to use closed system transfer devices (CSTDs), adapters and syringes containing polycarbonate or acrylonitrile-butadiene-styrene (ABS) prior to dilution in the infusion bag [see Dosage and Administration (2.4)].

If using a syringe to withdraw and transfer TREANDA Injection from the vial into the infusion bag, only use a polypropylene syringe with a metal needle and polypropylene hub to withdraw and transfer TREANDA Injection into the infusion bag. Polypropylene syringes are translucent in appearance.

TREANDA Injection and the reconstituted TREANDA for Injection have different concentrations of bendamustine hydrochloride. The concentration of bendamustine hydrochloride in the solution is 90 mg/mL and the concentration of bendamustine hydrochloride in the reconstituted solution of lyophilized powder is 5 mg/mL. Do not mix or combine the two formulations.

TREANDA Injection must be withdrawn and transferred for dilution in a biosafety cabinet (BSC) or containment isolator using a polypropylene syringe with a metal needle and a polypropylene hub.

If a CSTD or adapter that contains polycarbonate or ABS is used as supplemental protection prior to dilution^1, only use TREANDA for Injection, the lyophilized powder formulation [see How Supplied/Storage and Handling (16)].

2.2 Dosing Instructions for CLL

Recommended Dosage:

The recommended dose is 100 mg/m^2 administered intravenously over 30 minutes on Days 1 and 2 of a 28-day cycle, up to 6 cycles.

Dose Delays, Dose Modifications and Reinitiation of Therapy for CLL:

Delay TREANDA administration in the event of Grade 4 hematologic toxicity or clinically significant ≥ Grade 2 non-hematologic toxicity. Once non-hematologic toxicity has recovered to less than or equal to Grade 1 and/or the blood counts have improved [Absolute Neutrophil Count (ANC) ≥ 1 x 10^9/L, platelets ≥ 75 x 10^9/L], reinitiate TREANDA at the discretion of the treating physician. In addition, consider dose reduction. [see Warnings and Precautions (5.1)]

Dose modifications for hematologic toxicity: for Grade 3 or greater toxicity, reduce the dose to 50 mg/m^2 on Days 1 and 2 of each cycle; if Grade 3 or greater toxicity recurs, reduce the dose to 25 mg/m^2 on Days 1 and 2 of each cycle.

Dose modifications for non-hematologic toxicity: for clinically significant Grade 3 or greater toxicity, reduce the dose to 50 mg/m^2 on Days 1 and 2 of each cycle.

Consider dose re-escalation in subsequent cycles at the discretion of the treating physician.

2.3 Dosing Instructions for NHL

Recommended Dosage:

The recommended dose is 120 mg/m^2 administered intravenously over 60 minutes on Days 1 and 2 of a 21-day cycle, up to 8 cycles.

Dose Delays, Dose Modifications and Reinitiation of Therapy for NHL:

Delay TREANDA administration in the event of a Grade 4 hematologic toxicity or clinically significant greater than or equal to Grade 2 non-hematologic toxicity. Once non-hematologic toxicity has recovered to ≤ Grade 1 and/or the blood counts have improved [Absolute Neutrophil Count (ANC) ≥ 1 x 10^9/L, platelets ≥ 75 x 10^9/L], reinitiate TREANDA at the discretion of the treating physician. In addition, consider dose reduction. [see Warnings and Precautions (5.1)]

Dose modifications for hematologic toxicity: for Grade 4 toxicity, reduce the dose to 90 mg/m^2 on Days 1 and 2 of each cycle; if Grade 4 toxicity recurs, reduce the dose to 60 mg/m^2 on Days 1 and 2 of each cycle.

Dose modifications for non-hematologic toxicity: for Grade 3 or greater toxicity, reduce the dose to 90 mg/m^2 on Days 1 and 2 of each cycle; if Grade 3 or greater toxicity recurs, reduce the dose to 60 mg/m^2 on Days 1 and 2 of each cycle.

2.4 Preparation for Intravenous Administration

TREANDA is a hazardous drug. Follow applicable special handling and disposal procedures.^1

TREANDA Injection (45 mg/0.5 mL or 180 mg/2 mL solution)

TREANDA Injection must be diluted in a biosafety cabinet (BSC) or containment isolator.

- When preparing and transferring the concentrated TREANDA Injection solution into the infusion bag, do not use devices that contain polycarbonate or ABS. However, after dilution of TREANDA Injection into the infusion bag, devices that contain polycarbonate or ABS, including infusion sets, may be used.
  TREANDA Injection contains N,N-dimethylacetamide (DMA), which is incompatible with devices that contain polycarbonate or ABS. Devices, including CSTDs, adapters, and syringes that contain polycarbonate or ABS have been shown to dissolve when they come in contact with DMA which is present in the product. This incompatibility leads to device failure (e.g., leaking, breaking, or operational failure of CSTD components), possible product contamination, and potential serious adverse health consequences to the practitioner, including skin reactions; or to the patient, including but not limited to, the risk of small blood vessel blockage if they receive product contaminated with dissolved ABS or polycarbonate. Devices that are compatible for use in dilution of TREANDA Injection are available.
- If using a syringe to withdraw and transfer TREANDA Injection from the vial into the infusion bag, only use a polypropylene syringe with a metal needle and a polypropylene hub to withdraw and transfer TREANDA Injection into the infusion bag.
- Each vial of TREANDA Injection is intended for single dose only.
- Aseptically withdraw the volume needed for the required dose from the 90 mg/mL solution using a polypropylene syringe with a metal needle and a polypropylene hub.
- Immediately transfer the solution to a 500 mL infusion bag of 0.9% Sodium Chloride Injection, USP (normal saline). As an alternative to 0.9% Sodium Chloride Injection, USP (normal saline), a 500 mL infusion bag of 2.5% Dextrose/0.45% Sodium Chloride Injection, USP, may be considered. The resulting final concentration of bendamustine HCl in the infusion bag should be within 0.2 – 0.7 mg/mL.
- After dilution of TREANDA Injection into the infusion bag, devices that contain polycarbonate or ABS, including infusion sets, may be used.
- Visually inspect the filled syringe and the prepared infusion bag to ensure the lack of visible particulate matter prior to administration. The admixture should be a clear colorless to yellow solution.

Use either 0.9% Sodium Chloride Injection, USP, or 2.5% Dextrose/0.45% Sodium Chloride Injection, USP, for dilution, as outlined above. No other diluents have been shown to be compatible.

TREANDA for Injection (25 mg/vial or 100 mg/vial lyophilized powder)

If a closed system transfer device or adapter that contains polycarbonate or ABS is to be used as supplemental protection during preparation^1, only use TREANDA for Injection, the lyophilized formulation.

- Each vial of TREANDA for Injection is intended for single-dose only.
- Aseptically reconstitute each TREANDA for Injection vial as follows:
  - 25 mg TREANDA for Injection vial: Add 5 mL of only Sterile Water for Injection, USP.
  - 100 mg TREANDA for Injection vial: Add 20 mL of only Sterile Water for Injection, USP.
- Shake well to yield a clear, colorless to a pale yellow solution with a bendamustine HCl concentration of 5 mg/mL. The lyophilized powder should completely dissolve in 5 minutes. The reconstituted solution must be transferred to the infusion bag within 30 minutes of reconstitution. If particulate matter is observed, the reconstituted product should not be used.
- Aseptically withdraw the volume needed for the required dose (based on 5 mg/mL concentration) and immediately transfer to a 500 mL infusion bag of 0.9% Sodium Chloride Injection, USP (normal saline). As an alternative to 0.9% Sodium Chloride Injection, USP (normal saline), a 500 mL infusion bag of 2.5% Dextrose/0.45% Sodium Chloride Injection, USP, may be considered. The resulting final concentration of bendamustine HCl in the infusion bag should be within 0.2 to 0.6 mg/mL. After transferring, thoroughly mix the contents of the infusion bag.
- Visually inspect the filled syringe and the prepared infusion bag to ensure the lack of visible particulate matter prior to administration. The admixture should be a clear and colorless to slightly yellow solution.

Use Sterile Water for Injection, USP, for reconstitution and then either 0.9% Sodium Chloride Injection, USP, or 2.5% Dextrose/0.45% Sodium Chloride Injection, USP, for dilution, as outlined above. No other diluents have been shown to be compatible.

Parenteral drug products should be inspected visually for particulate matter and discoloration prior to administration whenever solution and container permit. Any unused solution should be discarded according to institutional procedures for antineoplastics.

2.5 Admixture Stability

TREANDA Injection and TREANDA for Injection contain no antimicrobial preservative. The admixture should be prepared as close as possible to the time of patient administration.

TREANDA Injection (45 mg/0.5 mL or 180 mg/2 mL solution)

Once diluted with either 0.9% Sodium Chloride Injection, USP, or 2.5% Dextrose/0.45% Sodium Chloride Injection, USP, the final admixture is stable for 24 hours stored under refrigerated conditions at 2°C to 8°C (36°F to 46°F) or for
2 hours when stored at room temperature (15°C to 30°C or 59°F to 86°F) and room light. Administration of diluted TREANDA Injection must be completed within this period.

TREANDA for Injection (25 mg/vial or 100 mg/vial lyophilized powder)

Once diluted with either 0.9% Sodium Chloride Injection, USP, or 2.5% Dextrose/0.45% Sodium Chloride Injection, USP, the final admixture is stable for 24 hours stored under refrigerated conditions at 2°C to 8°C (36°F to 46°F) or for
3 hours when stored at room temperature (15°C to 30°C or 59°F to 86°F) and room light. Administration of reconstituted and diluted TREANDA for Injection must be completed within this period.

3 DOSAGE FORMS AND STRENGTHS

- TREANDA Injection: 45 mg/0.5 mL or 180 mg/2 mL as a clear and colorless to yellow ready-to dilute solution in a single-dose vial.
- TREANDA for Injection: 25 mg or 100 mg white to off-white lyophilized powder in a single-dose vial for reconstitution.

4 CONTRAINDICATIONS

TREANDA is contraindicated in patients with a known hypersensitivity (e.g., anaphylactic and anaphylactoid reactions) to bendamustine. [see Warnings and Precautions (5.4)]

5 WARNINGS AND PRECAUTIONS

5.1 Myelosuppression

TREANDA caused severe myelosuppression (Grade 3-4) in 98% of patients in the two NHL studies [see Adverse Reactions (6.1)]. Three patients (2%) died from myelosuppression-related adverse reactions; one each from neutropenic sepsis, diffuse alveolar hemorrhage with Grade 3 thrombocytopenia, and pneumonia from an opportunistic infection (CMV).

Monitor complete blood counts, including leukocytes, platelets, hemoglobin (Hgb), and neutrophils frequently. In the clinical trials, blood counts were monitored every week initially. Hematologic nadirs were observed predominantly in the third week of therapy. Myelosuppression may require dose delays and/or subsequent dose reductions if recovery to the recommended values has not occurred by the first day of the next scheduled cycle. Prior to the initiation of the next cycle of therapy, the ANC should be ≥ 1 x 10^9/L and the platelet count should be ≥ 75 x 10^9/L. [see Dosage and Administration (2.2) and (2.3)]

5.2 Infections

Infection, including pneumonia, sepsis, septic shock, hepatitis and death has occurred in adult and pediatric patients in clinical trials and in postmarketing reports [see Adverse Reactions (6.1, 6.2)]. Patients with myelosuppression following treatment with TREANDA are more susceptible to infections. Advise patients with myelosuppression following TREANDA treatment to contact a physician if they have symptoms or signs of infection.

Patients treated with TREANDA are at risk for reactivation of infections including (but not limited to) hepatitis B, cytomegalovirus, Mycobacterium tuberculosis, and herpes zoster. Patients should undergo appropriate measures (including clinical and laboratory monitoring, prophylaxis, and treatment) for infection and infection reactivation prior to administration.

5.3 Progressive Multifocal Leukoencephalopathy (PML)

Progressive multifocal leukoencephalopathy (PML), including fatal cases, have occurred following treatment with bendamustine, primarily in combination with rituximab or obinutuzumab [see Adverse Reactions (6.2)]. Consider PML in the differential diagnosis in patients with new or worsening neurological, cognitive or behavioral signs or symptoms. If PML is suspected, withhold TREANDA treatment and perform appropriate diagnostic evaluations. Consider discontinuation or reduction of any concomitant chemotherapy or immunosuppressive therapy in patients who develop PML.

5.4 Anaphylaxis and Infusion Reactions

Infusion reactions to TREANDA have occurred commonly in clinical trials [see Adverse Reactions (6.1)]. Symptoms include fever, chills, pruritus and rash. In rare instances severe anaphylactic and anaphylactoid reactions have occurred, particularly in the second and subsequent cycles of therapy. Monitor clinically and discontinue drug for severe reactions. Ask patients about symptoms suggestive of infusion reactions after their first cycle of therapy. Patients who experience Grade 3 or worse allergic-type reactions should not be rechallenged. Consider measures to prevent severe reactions, including antihistamines, antipyretics and corticosteroids in subsequent cycles in patients who have experienced Grade 1 or 2 infusion reactions. Discontinue TREANDA for patients with Grade 4 infusion reactions. Consider discontinuation for Grade 3 infusions reactions as clinically appropriate considering individual benefits, risks, and supportive care.

5.5 Tumor Lysis Syndrome

Tumor lysis syndrome associated with TREANDA treatment has occurred in patients in clinical trials and in postmarketing reports [see Adverse Reactions (6.1)]. The onset tends to be within the first treatment cycle of TREANDA and, without intervention, may lead to acute renal failure and death. Preventive measures include vigorous hydration and close monitoring of blood chemistry, particularly potassium and uric acid levels. Allopurinol has also been used during the beginning of TREANDA therapy. However, there may be an increased risk of severe skin toxicity when TREANDA and allopurinol are administered concomitantly [see Warnings and Precautions (5.6)].

5.6 Skin Reactions

Fatal and serious skin reactions have been reported with TREANDA treatment in clinical trials and postmarketing safety reports, including toxic skin reactions [Stevens-Johnson Syndrome (SJS), toxic epidermal necrolysis (TEN), and drug reaction with eosinophilia and systemic symptoms (DRESS)], bullous exanthema, and rash [see Adverse Reactions (6.1, 6.2)]. Events occurred when TREANDA was given as a single agent and in combination with other anticancer agents or allopurinol.

Where skin reactions occur, they may be progressive and increase in severity with further treatment. Monitor patients with skin reactions closely. If skin reactions are severe or progressive, withhold or discontinue TREANDA.

5.7 Hepatotoxicity

Fatal and serious cases of liver injury have been reported with TREANDA [see Adverse Reactions (6.1)]. Combination therapy, progressive disease or reactivation of hepatitis B were confounding factors in some patients [see Warnings and Precautions (5.2)]. Most cases were reported within the first three months of starting therapy. Monitor liver chemistry tests prior to and during bendamustine therapy.

5.8 Other Malignancies

There are reports of pre-malignant and malignant diseases that have developed in patients who have been treated with TREANDA, including myelodysplastic syndrome, myeloproliferative disorders, acute myeloid leukemia, bronchial carcinoma, and non-melanoma skin cancer, including basal cell carcinoma and squamous cell carcinoma [see Adverse Reactions (6.2)].

Monitor patients for the development of secondary malignancies. Perform dermatologic evaluations during and after treatment with TREANDA.

5.9 Extravasation Injury

TREANDA extravasations have been reported in postmarketing resulting in hospitalizations from erythema, marked swelling, and pain [see Adverse Reactions (6.2)]. Assure good venous access prior to starting TREANDA infusion and monitor the intravenous infusion site for redness, swelling, pain, infection, and necrosis during and after administration of TREANDA.

5.10 Embryo-Fetal Toxicity

Based on findings from animal reproduction studies and the drug’s mechanism of action, TREANDA can cause fetal harm when administered to a pregnant woman. Single intraperitoneal doses of bendamustine (that approximated the maximum recommended human dose based on body surface area) to pregnant mice and rats during organogenesis caused adverse developmental outcomes, including an increase in resorptions, skeletal and visceral malformations, and decreased fetal body weights. Advise pregnant women of the potential risk to a fetus. Advise females of reproductive potential to use an effective method of contraception during treatment with TREANDA and for 6 months after the last dose. Advise males with female partners of reproductive potential to use effective contraception during treatment with TREANDA and for 3 months after the last dose [see Use in Specific Populations (8.1, 8.3) and Clinical Pharmacology (12.1)]

6 ADVERSE REACTIONS

The following clinically significant adverse reactions have been associated with TREANDA in clinical trials and are discussed in greater detail in other sections of the label.

- Myelosuppression [see Warnings and Precautions (5.1)]
- Infections [see Warnings and Precautions (5.2)]
- Progressive Multifocal Leukoencephalopathy [see Warnings and Precautions (5.3)]
- Anaphylaxis and Infusion Reactions [see Warnings and Precautions (5.4)]
- Tumor Lysis Syndrome [see Warnings and Precautions (5.5)]
- Skin Reactions [see Warnings and Precautions (5.6)]
- Hepatotoxicity [see Warnings and Precautions (5.7)]
- Other Malignancies [see Warnings and Precautions (5.8)]
- Extravasation Injury [see Warnings and Precautions (5.9)]

6.1 Clinical Trials Experience

Because clinical trials are conducted under widely varying conditions, adverse reaction rates observed in the clinical trials of a drug cannot be directly compared to rates in the clinical trials of another drug and may not reflect the rates observed in practice.

Chronic Lymphocytic Leukemia

The data described below reflect exposure to TREANDA in 153 patients. TREANDA was studied in an active-controlled, randomized trial. The population was 45-77 years of age, 63% male, 100% white, and had treatment naïve CLL. All patients started the study at a dose of 100 mg/m^2 intravenously over 30 minutes on Days 1 and 2 every 28 days.

Adverse reactions were reported according to NCI CTC v.2.0. In the randomized CLL clinical study, non-hematologic adverse reactions (any grade) in the TREANDA group that occurred with a frequency greater than 15% were pyrexia (24%), nausea (20%), and vomiting (16%).

Other adverse reactions seen frequently in one or more studies included asthenia, fatigue, malaise, and weakness; dry mouth; somnolence; cough; constipation; headache; mucosal inflammation and stomatitis.

Worsening hypertension was reported in 4 patients treated with TREANDA in the randomized CLL clinical study and in none treated with chlorambucil. Three of these 4 adverse reactions were described as a hypertensive crisis and were managed with oral medications and resolved.

The most frequent adverse reactions leading to study withdrawal for patients receiving TREANDA were hypersensitivity (2%) and pyrexia (1%).

Table 1 contains the treatment emergent adverse reactions, regardless of attribution, that were reported in ≥ 5% of patients in either treatment group in the randomized CLL clinical study.

Table 1: Non- Hematologic Adverse Reactions Occurring in Randomized CLL Clinical Study in at Least 5% of Patients

 |  | Number (%) of patients
 |  | TREANDA (N=153) |  | Chlorambucil (N=143)
Body System/Adverse Reaction |  | All Grades | Grade 3/4 | All Grades | Grade 3/4
Total number of patients with at least 1 adverse reaction |  | 121 (79) | 52 (34) | 96 (67) | 25 (17)
Gastrointestinal; disorders; Nausea; Vomiting; Diarrhea |  | 31 (20); 24 (16); 14 (9) | 1 (<1); 1 (<1); 2 (1) | 21 (15); 9 (6); 5 (3) | 1 (<1); 0; 0
General disorders and; administration site; conditions; Pyrexia; Fatigue; Asthenia; Chills |  | 36 (24); 14 (9); 13 (8); 9 (6) | 6 (4); 2 (1); 0; 0 | 8 (6); 8 (6); 6 (4); 1 (<1) | 2 (1); 0; 0; 0
Immune system; disorders; Hypersensitivity |  | 7 (5) | 2 (1) | 3 (2) | 0
Infections and; infestations; Nasopharyngitis; Infection; Herpes simplex |  | 10 (7); 9 (6); 5 (3) | 0; 3 (2); 0 | 12 (8); 1 (<1); 7 (5) | 0; 1 (<1); 0
Investigations; Weight decreased |  | 11 (7) | 0 | 5 (3) | 0
Metabolism and nutrition disorders; Hyperuricemia |  | 11 (7) | 3 (2) | 2 (1) | 0
Respiratory, thoracic and mediastinal disorders; Cough |  | 6 (4) | 1 (<1) | 7 (5) | 1 (<1)
Skin and subcutaneous tissue disorders; Rash; Pruritus |  | 12 (8); 8 (5) | 4 (3); 0 | 7 (5); 2 (1) | 3 (2); 0

The Grade 3 and 4 hematology laboratory test values by treatment group in the randomized CLL clinical study are described in Table 2. These findings confirm the myelosuppressive effects seen in patients treated with TREANDA. Red blood cell transfusions were administered to 20% of patients receiving TREANDA compared with 6% of patients receiving chlorambucil.

Table 2: Incidence of Hematology Laboratory Abnormalities in Patients Who Received TREANDA or Chlorambucil in the Randomized CLL Clinical Study
 | TREANDA N=150 |  | Chlorambucil N=141
Laboratory Abnormality | All Grades n (%) | Grade 3/4 n (%) | All Grades n (%) | Grade 3/4 n (%)
Hemoglobin Decreased | 134 (89) | 20 (13) | 115 (82) | 12 (9)
Platelets Decreased | 116 (77) | 16 (11) | 110 (78) | 14 (10)
Leukocytes Decreased | 92 (61) | 42 (28) | 26 (18) | 4 (3)
Lymphocytes Decreased | 102 (68) | 70 (47) | 27 (19) | 6 (4)
Neutrophils Decreased | 113 (75) | 65 (43) | 86 (61) | 30 (21)

In the randomized CLL trial, 34% of patients had bilirubin elevations, some without associated significant elevations in AST and ALT. Grade 3 or 4 increased bilirubin occurred in 3% of patients. Increases in AST and ALT of Grade 3 or 4 were limited to 1% and 3% of patients, respectively. Patients treated with TREANDA may also have changes in their creatinine levels. If abnormalities are detected, monitoring of these parameters should be continued to ensure that further deterioration does not occur.

Non-Hodgkin Lymphoma

The data described below reflect exposure to TREANDA in 176 patients with indolent B-cell NHL treated in two single-arm studies. The population was 31-84 years of age, 60% male, and 40% female. The race distribution was 89% White, 7% Black, 3% Hispanic, 1% other, and <1% Asian. These patients received TREANDA at a dose of 120 mg/m^2 intravenously on Days 1 and 2 for up to eight 21-day cycles.

The adverse reactions occurring in at least 5% of the NHL patients, regardless of severity, are shown in Table 3. The most common non-hematologic adverse reactions (≥30%) were nausea (75%), fatigue (57%), vomiting (40%), diarrhea (37%) and pyrexia (34%). The most common non-hematologic Grade 3 or 4 adverse reactions (≥5%) were fatigue (11%), febrile neutropenia (6%), and pneumonia, hypokalemia and dehydration, each reported in 5% of patients.

Table 3: Non-Hematologic Adverse Reactions Occurring in at Least 5% of NHL Patients Treated with TREANDA (N=176)
Body System/ Adverse | Number (%) of patients*
Reaction | All Grades | Grade 3/4
Total number of patients with at least 1 adverse reaction | 176 (100) | 94 (53)
Cardiac disorders
Tachycardia | 13 (7) | 0
Gastrointestinal disorders
Nausea | 132 (75) | 7 (4)
Vomiting | 71 (40) | 5 (3)
Diarrhea | 65 (37) | 6 (3)
Constipation | 51 (29) | 1 (<1)
Stomatitis | 27 (15) | 1 (<1)
Abdominal pain | 22 (13) | 2 (1)
Dyspepsia | 20 (11) | 0
Gastroesophageal reflux disease | 18 (10) | 0
Dry mouth | 15 (9) | 1 (<1)
Abdominal pain upper | 8 (5) | 0
Abdominal distension | 8 (5) | 0
General disorders and administration
site conditions
Fatigue | 101 (57) | 19 (11)
Pyrexia | 59 (34) | 3 (2)
Chills | 24 (14) | 0
Edema peripheral | 23 (13) | 1 (<1)
Asthenia | 19 (11) | 4 (2)
Chest pain | 11 (6) | 1 (<1)
Infusion site pain | 11 (6) | 0
Pain | 10 (6) | 0
Catheter site pain | 8 (5) | 0
Infections and infestations
Herpes zoster | 18 (10) | 5 (3)
Upper respiratory tract infection | 18 (10) | 0
Urinary tract infection | 17 (10) | 4 (2)
Sinusitis | 15 (9) | 0
Pneumonia | 14 (8) | 9 (5)
Febrile neutropenia | 11 (6) | 11 (6)
Oral candidiasis | 11 (6) | 2 (1)
Nasopharyngitis | 11 (6) | 0
Investigations
Weight decreased | 31 (18) | 3 (2)
Metabolism and nutrition disorders
Anorexia | 40 (23) | 3 (2)
Dehydration | 24 (14) | 8 (5)
Decreased appetite | 22 (13) | 1 (<1)
Hypokalemia | 15 (9) | 9 (5)
Musculoskeletal and connective tissue
disorders
Back pain | 25 (14) | 5 (3)
Arthralgia | 11 (6) | 0
Pain in extremity | 8 (5) | 2 (1)
Bone pain | 8 (5) | 0
Nervous system disorders
Headache | 36 (21) | 0
Dizziness | 25 (14) | 0
Dysgeusia | 13 (7) | 0
Psychiatric disorders
Insomnia | 23 (13) | 0
Anxiety | 14 (8) | 1 (<1)
Depression | 10 (6) | 0
Respiratory, thoracic and mediastinal
disorders
Cough | 38 (22) | 1 (<1)
Dyspnea | 28 (16) | 3 (2)
Pharyngolaryngeal pain | 14 (8) | 1 (<1)
Wheezing | 8 (5) | 0
Nasal congestion | 8 (5) | 0
Skin and subcutaneous tissue disorders
Rash | 28 (16) | 1 (<1)
Pruritus | 11 (6) | 0
Dry skin | 9 (5) | 0
Night sweats | 9 (5) | 0
Hyperhidrosis | 8 (5) | 0
Vascular disorders
Hypotension | 10 (6) | 2 (1)
*Patients may have reported more than 1 adverse reaction.
NOTE: Patients counted only once in each adverse reaction category and once in each body system category.

Hematologic toxicities, based on laboratory values and CTC grade, in NHL patients treated in both single arm studies combined are described in Table 4. Clinically important chemistry laboratory values that were new or worsened from baseline and occurred in >1% of patients at Grade 3 or 4, in NHL patients treated in both single arm studies combined were hyperglycemia (3%), elevated creatinine (2%), hyponatremia (2%), and hypocalcemia (2%).

Table 4: Incidence of Hematology Laboratory Abnormalities in Patients Who Received TREANDA in the NHL Studies
Hematology variable | Percent of patients
Hematology variable | All Grades | Grade 3/4
Lymphocytes Decreased | 99 | 94
Leukocytes Decreased | 94 | 56
Hemoglobin Decreased | 88 | 11
Neutrophils Decreased | 86 | 60
Platelets Decreased | 86 | 25

In both studies, serious adverse reactions, regardless of causality, were reported in 37% of patients receiving TREANDA. The most common serious adverse reactions occurring in ≥5% of patients were febrile neutropenia and pneumonia. Other important serious adverse reactions reported in clinical trials and/or postmarketing experience were acute renal failure, cardiac failure, hypersensitivity, skin reactions, pulmonary fibrosis, and myelodysplastic syndrome.

Serious drug-related adverse reactions reported in clinical trials included myelosuppression, infection, pneumonia, tumor lysis syndrome and infusion reactions. Adverse reactions occurring less frequently but possibly related to TREANDA treatment were hemolysis, dysgeusia/taste disorder, atypical pneumonia, sepsis, herpes zoster, erythema, dermatitis, and skin necrosis.

6.2 Postmarketing Experience

The following adverse reactions have been identified during post-approval use of TREANDA. Because these reactions are reported voluntarily from a population of uncertain size, it is not always possible to reliably estimate their frequency or establish a causal relationship to drug exposure.

Blood and lymphatic systems disorders: Pancytopenia

Cardiovascular disorders: Atrial fibrillation, congestive heart failure (some fatal), myocardial infarction (some fatal), palpitation

General disorders and administration site conditions: Injection site reactions (including phlebitis, pruritus, irritation, pain, swelling), infusion site reactions (including phlebitis, pruritus, irritation, pain, swelling)

Immune system disorders: Anaphylaxis

Infections and infestations: Pneumocystis jiroveci pneumonia, progressive multifocal leukoencephalopathy (PML)

Renal and urinary disorders: Nephrogenic diabetes insipidus (NDI)

Respiratory, thoracic and mediastinal disorders: Pneumonitis

Skin and subcutaneous tissue disorders: Drug reaction with eosinophilia and systemic symptoms (DRESS), non-melanoma skin cancer (NMSC), Stevens-Johnson syndrome (SJS), toxic epidermal necrolysis (TEN)

7 DRUG INTERACTIONS

7.1 Effect of Other Drugs on TREANDA

CYP1A2 Inhibitors

The coadministration of TREANDA with CYP1A2 inhibitors may increase bendamustine plasma concentrations and may result in increased incidence of adverse reactions with TREANDA [see Clinical Pharmacology (12.3)]. Consider alternative therapies that are not CYP1A2 inhibitors during treatment with TREANDA.

CYP1A2 Inducers

The coadministration of TREANDA with CYP1A2 inducers may decrease bendamustine plasma concentrations and may result in decreased efficacy of TREANDA [see Clinical Pharmacology (12.3)]. Consider alternative therapies that are not CYP1A2 inducers during treatment with TREANDA.

8 USE IN SPECIFIC POPULATIONS

8.1 Pregnancy

Risk Summary

In animal reproduction studies, intraperitoneal administration of bendamustine to pregnant mice and rats during organogenesis at doses 0.6 to 1.8 times the maximum recommended human dose (MRHD) resulted in embryo-fetal and/or infant mortality, structural abnormalities, and alterations to growth (see Data). There are no available data on bendamustine hydrochloride use in pregnant women to evaluate for a drug-associated risk of major birth defects, miscarriage or adverse maternal or fetal outcomes. Advise pregnant women of the potential risk to a fetus.

The estimated background risk of major birth defects and miscarriage for the indicated population is unknown. All pregnancies have a background risk of birth defect, loss, or other adverse outcomes. In the U.S. general population, the estimated background risk of major birth defects and miscarriage in clinically recognized pregnancies is 2 to 4% and 15 to 20%, respectively.

Data

Animal data

Bendamustine hydrochloride was intraperitoneally administered once to mice from 210 mg/m^2 (approximately 1.8 times the MRHD) during organogenesis and caused an increase in resorptions, skeletal and visceral malformations (exencephaly, cleft palates, accessory rib, and spinal deformities), and decreased fetal body weights. This dose did not appear to be maternally toxic and lower doses were not evaluated. Repeat intraperitoneal administration of bendamustine hydrochloride to mice on gestation days 7 to 11 resulted in an increase in resorptions from 75 mg/m^2 (approximately 0.6 times the MRHD) and an increase in abnormalities from 112.5 mg/m^2 (approximately 0.9 times the MRHD), similar to those seen after a single intraperitoneal administration.

Bendamustine hydrochloride was intraperitoneally administered once to rats from 120 mg/m^2 (approximately the MRHD) on gestation days 4, 7, 9, 11, or 13 and caused embryo and fetal lethality as indicated by increased resorptions and a decrease in live fetuses. A significant increase in external (effect on tail, head, and herniation of external organs [exomphalos]) and internal (hydronephrosis and hydrocephalus) malformations were seen in dosed rats.

8.2 Lactation

Risk Summary

There are no data on the presence of bendamustine hydrochloride or its metabolites in either human or animal milk, the effects on the breastfed child, or the effects on milk production. Because of the potential for serious adverse reactions in the breastfed child, advise patients that breastfeeding is not recommended during treatment with TREANDA, and for 1 week after the last dose.

8.3 Females and Males of Reproductive Potential

TREANDA can cause fetal harm when administered to a pregnant woman [see Use in Specific Populations (8.1)].

Pregnancy Testing

Pregnancy testing is recommended for females of reproductive potential prior to initiation of treatment with TREANDA.

Contraception

Females

TREANDA can cause embryo-fetal harm when administered to pregnant women [see Use in Specific Populations (8.1)]. Advise female patients of reproductive potential to use effective contraception during treatment with TREANDA and for 6 months after the last dose.

Males

Based on genotoxicity findings, advise males with female partners of reproductive potential to use effective contraception during treatment with TREANDA and for 3 months after the last dose [see Nonclinical Toxicology (13.1)].

Infertility

Males

Based on findings from clinical studies, TREANDA may impair male fertility. Impaired spermatogenesis, azoospermia, and total germinal aplasia have been reported in male patients treated with alkylating agents, especially in combination with other drugs. In some instances spermatogenesis may return in patients in remission, but this may occur only several years after intensive chemotherapy has been discontinued. Patients should be warned of the potential risk to their reproductive capacities.

Based on findings from animal studies, TREANDA may impair male fertility due to an increase in morphologically abnormal spermatozoa. The long-term effects of TREANDA on male fertility, including the reversibility of adverse effects, have not been studied [see Nonclinical Toxicology (13.1)].

8.4 Pediatric Use

Safety and effectiveness in pediatric patients have not been established.

Safety, pharmacokinetics and efficacy were assessed in a single open-label trial (NCT01088984) in patients aged 1 to 19 years with relapsed or refractory acute leukemia, including 27 patients with acute lymphocytic leukemia (ALL) and 16 patients with acute myeloid leukemia (AML). TREANDA was administered as an intravenous infusion over 60 minutes on Days 1 and 2 of each 21-day cycle. There was no treatment response (CR+ CRp) in any patient in the Phase 2 portion of the trial at a dose of 120 mg/m^2. However, 2 patients with ALL achieved CR at a dose of 90 mg/m^2 in the Phase 1 portion of the study. The safety profile in these patients was consistent with that seen in adults, and no new safety signals were identified.

The pharmacokinetics of bendamustine in 43 patients, aged 1 to 19 years (median age of 10 years) were within range of values previously observed in adults given the same dose based on body surface area.

8.5 Geriatric Use

No overall differences in safety were observed between patients ≥65 years of age and younger patients. Efficacy was lower in patients 65 and over with CLL receiving TREANDA based upon an overall response rate of 47% for patients 65 and over and 70% for younger patients. Progression free survival was also longer in younger patients with CLL receiving TREANDA (19 months vs. 12 months). No overall differences in efficacy in patients with non-Hodgkin Lymphoma were observed between geriatric patients and younger patients.

8.6 Renal Impairment

Do not use TREANDA in patients with creatinine clearance (CLcr) < 30 mL/min. [see Clinical Pharmacology (12.3)]

8.7 Hepatic Impairment

Do not use TREANDA in patients with AST or ALT 2.5-10 × upper limit of normal (ULN) and total bilirubin 1.5-3 × ULN, or total bilirubin > 3 × ULN [see Clinical Pharmacology (12.3)]

10 OVERDOSAGE

The intravenous LD50 of bendamustine HCl is 240 mg/m^2 in the mouse and rat. Toxicities included sedation, tremor, ataxia, convulsions and respiratory distress.

Across all clinical experience, the reported maximum single dose received was 280 mg/m^2. Three of four patients treated at this dose showed ECG changes considered dose-limiting at 7 and 21 days post-dosing. These changes included QT prolongation (one patient), sinus tachycardia (one patient), ST and T wave deviations (two patients) and left anterior fascicular block (one patient). Cardiac enzymes and ejection fractions remained normal in all patients.

No specific antidote for TREANDA overdose is known. Management of overdosage should include general supportive measures, including monitoring of hematologic parameters and ECGs.

11 DESCRIPTION

TREANDA (bendamustine hydrochloride) is an alkylating agent. The chemical name of bendamustine hydrochloride is 1H-benzimidazole-2-butanoic acid, 5-[bis(2-chloroethyl)amino]-1 methyl-, monohydrochloride. Its empirical molecular formula is C16H21Cl2N3O2 ∙ HCl, and the molecular weight is 394.7. Bendamustine hydrochloride contains a mechlorethamine group and a benzimidazole heterocyclic ring with a butyric acid substituent, and has the following structural formula:

TREANDA Injection (45 mg/0.5 mL or 180 mg/2 mL solution)

TREANDA (bendamustine HCl) Injection for intravenous use is supplied as a sterile clear colorless to yellow solution in a single-dose vial. Each 0.5 mL vial contains 45 mg of bendamustine hydrochloride, 162 mg of Propylene Glycol, USP and 293 mg of N,N-Dimethylacetamide, EP. Each 2 mL vial contains 180 mg of bendamustine hydrochloride, 648 mg of Propylene Glycol, USP and 1172 mg of N,N-Dimethylacetamide, EP. An overfill of 0.2 mL is included in each vial.

TREANDA for Injection (25 mg/vial or 100 mg/vial lyophilized powder)

TREANDA (bendamustine HCl) for Injection for intravenous use is supplied as a sterile non-pyrogenic white to off-white lyophilized powder in a single-dose vial. Each 25-mg vial contains 25 mg of bendamustine hydrochloride and 42.5 mg of mannitol, USP. Each 100-mg vial contains 100 mg of bendamustine hydrochloride and 170 mg of mannitol, USP. The pH of the reconstituted solution is 2.5 to 3.5.

12 CLINICAL PHARMACOLOGY

12.1 Mechanism of Action

Bendamustine is a bifunctional mechlorethamine derivative containing a purine-like benzimidazole ring. Mechlorethamine and its derivatives form electrophilic alkyl groups. These groups form covalent bonds with electron-rich nucleophilic moieties, resulting in interstrand DNA crosslinks. The bifunctional covalent linkage can lead to cell death via several pathways. Bendamustine is active against both quiescent and dividing cells. The exact mechanism of action of bendamustine remains unknown.

12.2 Pharmacodynamics

Based on the pharmacokinetics/pharmacodynamics analyses of data from adult NHL patients, nausea increased with increasing bendamustine Cmax.

Cardiac Electrophysiology

The effect of bendamustine on the QTc interval was evaluated in 53 patients with indolent NHL and mantle cell lymphoma on Day 1 of Cycle 1 after administration of rituximab at 375 mg/m^2 intravenous infusion followed by a 30-minute intravenous infusion of bendamustine at 90 mg/m^2/day. No mean changes greater than 20 milliseconds were detected up to one hour post-infusion. The potential for delayed effects on the QT interval after one hour was not evaluated.

12.3 Pharmacokinetics

Absorption

Following a single IV dose of bendamustine hydrochloride Cmax typically occurred at the end of infusion. The dose proportionality of bendamustine has not been studied.

Distribution

The protein binding of bendamustine ranged from 94 to 96% and was concentration independent from 1 to 50 µg/mL. The blood to plasma concentration ratios in human blood ranged from 0.84 to 0.86 over a concentration range of 10 to 100 µg/mL.

The mean steady-state volume of distribution (Vss) of bendamustine was approximately 20 to 25 L.

Elimination

After a single intravenous dose of 120 mg/m^2 of bendamustine over 1 hour, the intermediate half-life (t½) of the parent compound is approximately 40 minutes. The mean terminal elimination t½ of two active metabolites, γ-hydroxybendamustine (M3) and N desmethylbendamustine (M4) are approximately 3 hours and 30 minutes, respectively. Bendamustine clearance in humans is approximately 700 mL/min.

Metabolism

Bendamustine is extensively metabolized via hydrolytic, oxidative, and conjugative pathways. Bendamustine is primarily metabolized via hydrolysis to monohydroxy (HP1) and dihydroxy-bendamustine (HP2) metabolites with low cytotoxic activity in vitro. Two active minor metabolites, M3 and M4, are primarily formed via CYP1A2 in vitro. M3 and M4 concentrations in plasma are 1/10th and 1/100th that of the parent compound, respectively.

Excretion

Following IV infusion of radiolabeled bendamustine hydrochloride in cancer patients, approximately 76% of the dose was recovered. Approximately 50% of the dose was recovered in the urine (3.3% unchanged) and approximately 25% of the dose was recovered in the feces. Less than 1% of the dose was recovered in the urine as M3 and M4, and less than 5% of the dose was recovered in the urine as HP2.

Specific Populations

No clinically meaningful effects on the pharmacokinetics of bendamustine were observed based on age (31 to 84 years), sex, mild to moderate renal impairment (CLcr ≥ 30 mL/min), or hepatic impairment with total bilirubin 1.5 < ULN and AST or ALT < 2.5 × ULN. The effects of severe renal impairment (CLcr < 30 mL/min), or hepatic impairment with total bilirubin 1.5-3 × ULN and AST or ALT 2.5-10 × ULN or total bilirubin > 3 × ULN on the pharmacokinetics of bendamustine is unknown.

Race/Ethnicity
Exposures in Japanese subjects (n=6) were 40% higher than that in non-Japanese subjects receiving the same dose. The clinical importance of this difference on the safety and efficacy of bendamustine hydrochloride in Japanese subjects has not been established.

Drug Interaction Studies

In Vitro Studies

Effect of Bendamustine on CYP Substrates

Bendamustine did not inhibit CYP1A2, 2C9/10, 2D6, 2E1, or 3A4/5. Bendamustine did not induce metabolism of CYP1A2, CYP2A6, CYP2B6, CYP2C8, CYP2C9, CYP2C19, CYP2E1, or CYP3A4/5.

Effect of Transporters on Bendamustine Hydrochloride

Bendamustine is a substrate of P-glycoprotein and breast cancer resistance protein (BCRP).

13 NONCLINICAL TOXICOLOGY

13.1 Carcinogenesis, Mutagenesis, Impairment of Fertility

Bendamustine was carcinogenic in mice. After intraperitoneal injections at 37.5 mg/m^2/day (the lowest dose tested, approximately 0.3 times the maximum recommended human dose [MRHD])) and 75 mg/m^2/day (approximately 0.6 times the MRHD) for 4 days, peritoneal sarcomas in female AB/Jena mice were produced. Oral administration at 187.5 mg/m^2/day (the only dose tested, approximately 1.6 times the MRHD) for 4 days induced mammary carcinomas and pulmonary adenomas.

Bendamustine is a mutagen and clastogen. In a bacterial reverse mutation assay (Ames assay), bendamustine was shown to increase revertant frequency in the absence and presence of metabolic activation. Bendamustine was clastogenic in human lymphocytes in vitro, and in rat bone marrow cells in vivo (increase in micronucleated polychromatic erythrocytes) from 37.5 mg/m^2 (the lowest dose tested, approximately 0.3 times the MRHD).

Bendamustine induced morphologic abnormalities in spermatozoa in mice. Following tail vein injection of bendamustine at 120 mg/m^2 or a saline control on days 1 and 2 for a total of 3 weeks, the number of spermatozoa with morphologic abnormalities was 16% higher in the bendamustine-treated group as compared to the saline control group.

14 CLINICAL STUDIES

14.1 Chronic Lymphocytic Leukemia (CLL)

The safety and efficacy of TREANDA were evaluated in an open-label, randomized, controlled multicenter trial comparing TREANDA to chlorambucil. The trial was conducted in 301 previously-untreated patients with Binet Stage B or C (Rai Stages I - IV) CLL requiring treatment. Need-to-treat criteria included hematopoietic insufficiency, B-symptoms, rapidly progressive disease or risk of complications from bulky lymphadenopathy. Patients with autoimmune hemolytic anemia or autoimmune thrombocytopenia, Richter’s syndrome, or transformation to prolymphocytic leukemia were excluded from the study.

The patient populations in the TREANDA and chlorambucil treatment groups were balanced with regard to the following baseline characteristics: age (median 63 vs. 66 years), gender (63% vs. 61% male), Binet stage (71% vs. 69% Binet B), lymphadenopathy (79% vs. 82%), enlarged spleen (76% vs. 80%), enlarged liver (48% vs. 46%), hypercellular bone marrow (79% vs. 73%), “B” symptoms (51% vs. 53%), lymphocyte count (mean 65.7x10^9/L vs. 65.1x10^9/L), and serum lactate dehydrogenase concentration (mean 370.2 vs. 388.4 U/L). Ninety percent of patients in both treatment groups had immuno-phenotypic confirmation of CLL (CD5, CD23 and either CD19 or CD20 or both).

Patients were randomly assigned to receive either TREANDA at 100 mg/m^2, administered intravenously over a period of 30 minutes on Days 1 and 2 or chlorambucil at 0.8 mg/kg (Broca’s normal weight) administered orally on Days 1 and 15 of each 28-day cycle. Efficacy endpoints of objective response rate and progression-free survival were calculated using a pre-specified algorithm based on NCI working group criteria for CLL.

The results of this open-label randomized study demonstrated a higher rate of overall response and a longer progression-free survival for TREANDA compared to chlorambucil (see Table 5). Survival data are not mature.

Table 5: Efficacy Data for CLL
 | TREANDA; (N=153) | Chlorambucil; (N=148) | p-value
Response Rate n (%)
Overall response rate | 90 (59) | 38 (26) | <0.0001
(95% CI) | (51.0, 66.6) | (18.6, 32.7)
Complete response (CR)* | 13 (8) | 1 (<1)
Nodular partial response (nPR)** | 4 (3) | 0
Partial response (PR)† | 73 (48) | 37 (25)
Progression-Free Survival††
Median, months (95% CI) | 18 (11.7, 23.5) | 6 (5.6, 8.6)
Hazard ratio (95% CI) | 0.27 (0.17, 0.43) |  | <0.0001

CI = confidence interval

* CR was defined as peripheral lymphocyte count ≤ 4.0 x 10^9/L, neutrophils ≥ 1.5 x 10^9/L, platelets >100 x 10^9/L, hemoglobin > 110g/L, without transfusions, absence of palpable hepatosplenomegaly, lymph nodes ≤ 1.5 cm, < 30% lymphocytes without nodularity in at least a normocellular bone marrow and absence of “B” symptoms. The clinical and laboratory criteria were required to be maintained for a period of at least 56 days.

** nPR was defined as described for CR with the exception that the bone marrow biopsy shows persistent nodules.

† PR was defined as ≥ 50% decrease in peripheral lymphocyte count from the pretreatment baseline value, and either ≥50% reduction in lymphadenopathy, or ≥50% reduction in the size of spleen or liver, as well as one of the following hematologic improvements: neutrophils ≥ 1.5 x 10^9/L or 50% improvement over baseline, platelets >100 x 10^9/L or 50% improvement over baseline, hemoglobin >110g/L or 50% improvement over baseline without transfusions, for a period of at least 56 days.

†† PFS was defined as time from randomization to progression or death from any cause.

Kaplan-Meier estimates of progression-free survival comparing TREANDA with chlorambucil are shown in Figure 1.

14.2 Non-Hodgkin Lymphoma (NHL)

The efficacy of TREANDA was evaluated in a single arm study of 100 patients with indolent B-cell NHL that had progressed during or within six months of treatment with rituximab or a rituximab-containing regimen. Patients were included if they relapsed within 6 months of either the first dose (monotherapy) or last dose (maintenance regimen or combination therapy) of rituximab. All patients received TREANDA intravenously at a dose of 120 mg/m^2, on Days 1 and 2 of a 21-day treatment cycle. Patients were treated for up to 8 cycles.

The median age was 60 years, 65% were male, and 95% had a baseline WHO performance status of 0 or 1. Major tumor subtypes were follicular lymphoma (62%), diffuse small lymphocytic lymphoma (21%), and marginal zone lymphoma (16%). Ninety-nine percent of patients had received previous chemotherapy, 91% of patients had received previous alkylator therapy, and 97% of patients had relapsed within 6 months of either the first dose (monotherapy) or last dose (maintenance regimen or combination therapy) of rituximab.

Efficacy was based on the assessments by a blinded independent review committee (IRC) and included overall response rate (complete response + complete response unconfirmed + partial response) and duration of response (DR) as summarized in Table 6.

Table 6: Efficacy Data for NHL*
 | TREANDA (N=100)
Response Rate (%)
Overall response rate (CR+CRu+PR) | 74
(95% CI) | (64.3, 82.3)
Complete response (CR) | 13
Complete response unconfirmed (CRu) | 4
Partial response (PR) | 57
Duration of Response (DR)
Median, months (95% CI) | 9.2 months (7.1, 10.8)
CI = confidence interval
*IRC assessment was based on modified International Working Group response criteria (IWG-RC). Modifications to IWG-RC specified that a persistently positive bone marrow in patients who met all other criteria for CR would be scored as PR. Bone marrow sample lengths were not required to be ≥20 mm.

15 REFERENCES

1. OSHA Hazardous Drugs. OSHA. http://www.osha.gov/SLTC/hazardousdrugs/index.html

16 HOW SUPPLIED/STORAGE AND HANDLING

Safe Handling and Disposal

TREANDA (bendamustine hydrochloride) is a hazardous drug. Follow applicable special handling and disposal procedures^1. Care should be exercised in the handling and preparation of solutions prepared from TREANDA Injection and TREANDA for Injection. The use of gloves and safety glasses is recommended to avoid exposure in case of breakage of the vial or other accidental spillage. If gloves come in contact with TREANDA Injection prior to dilution, remove gloves and follow disposal procedures^1. If a solution of TREANDA (bendamustine hydrochloride) contacts the skin, wash the skin immediately and thoroughly with soap and water. If TREANDA (bendamustine hydrochloride) contacts the mucous membranes, flush thoroughly with water.

How Supplied

TREANDA (bendamustine hydrochloride) Injection is supplied as a 90 mg/mL clear colorless to yellow solution in individual cartons as follows:

- NDC 63459-395-02: 45 mg/0.5 mL of solution in an amber single-dose vial
- NDC 63459-396-02: 180 mg/2 mL of solution in an amber single-dose vial

TREANDA (bendamustine hydrochloride) for Injection is supplied in individual cartons as follows:

- NDC 63459-390-08: 25 mg white to off-white lyophilized powder in a 8 mL amber single-dose vial
- NDC 63459-391-20: 100 mg white to off-white lyophilized powder in a 20 mL amber single-dose vial

Storage

TREANDA Injection (45 mg/0.5 mL or 180 mg/2 mL solution)

Store TREANDA Injection in refrigerator 2°C to 8°C (36°F to 46°F). Retain in original package until time of use to protect from light.

TREANDA for Injection (25 mg/vial or 100 mg/vial lyophilized powder)

TREANDA for Injection may be stored up to 25°C (77°F) with excursions permitted up to 30°C (86°F) (see USP Controlled Room Temperature). Retain in original package until time of use to protect from light.

17 PATIENT COUNSELING INFORMATION

Allergic (Hypersensitivity) Reactions

Inform patients of the possibility of mild or serious allergic reactions and to immediately report rash, facial swelling, or difficulty breathing during or soon after infusion [see Warnings and Precautions (5.4)].

Myelosuppression

Inform patients of the likelihood that TREANDA will cause a decrease in white blood cells, platelets, and red blood cells, and the need for frequent monitoring of blood counts. Advise patients to report shortness of breath, significant fatigue, bleeding, fever, or other signs of infection [see Warnings and Precautions (5.1)].

Progressive Multifocal Leukoencephalopathy (PML)

Inform patients to immediately contact their healthcare provider if they experience confusion, memory loss, trouble thinking, difficulty talking or walking, vision loss or other neurological or cognitive symptoms [see Warnings and Precautions (5.3)].

Hepatotoxicity

Inform patients of the possibility of developing liver function abnormalities and serious hepatic toxicity. Advise patients to immediately contact their health care provider if signs of liver failure occur, including jaundice, anorexia, bleeding or bruising [see Warnings and Precautions (5.7)].

Fatigue

Advise patients that TREANDA may cause tiredness and to avoid driving any vehicle or operating any dangerous tools or machinery if they experience this side effect [see Adverse Reactions (6.1)].

Nausea and Vomiting

Advise patients that TREANDA may cause nausea and/or vomiting. Patients should report nausea and vomiting so that symptomatic treatment may be provided [see Adverse Reactions (6.1)].

Diarrhea

Advise patients that TREANDA may cause diarrhea. Patients should report diarrhea to the physician so that symptomatic treatment may be provided [see Adverse Reactions (6.1)].

Rash

Advise patients that a rash or itching may occur during treatment with TREANDA. Advise patients to immediately report severe or worsening rash or itching [see Warnings and Precautions (5.6)].

Non-Melanoma Skin Cancer (NMSC)

Advise patients to undergo regular skin cancer screenings, and to report any suspicious skin changes to their healthcare provider [see Warnings and Precautions (5.8)].

Embryo-Fetal Toxicity

Advise pregnant women and females of reproductive potential of the potential risk to a fetus. Advise females to inform their healthcare provider of a known or suspected pregnancy [see Warnings and Precautions (5.10), Use in Specific Populations (8.1, 8.3), and Nonclinical Toxicology (13.1)]. Advise female patients of reproductive potential to use effective contraception during treatment with TREANDA and for 6 months after the last dose [see Use in Specific Populations (8.1, 8.3)]. Advise males with female partners of reproductive potential to use effective contraception during treatment with TREANDA and for 3 months after the last dose [see Use in Specific Populations (8.3), and Nonclinical Toxicology (13.1)].

Lactation

Advise females not to breastfeed during treatment with TREANDA and for 1 week after the last dose [see Use in Specific Populations (8.2)].

Infertility

Advise males of reproductive potential that TREANDA may impair fertility [see Use in Specific Populations (8.3)].

Manufactured for:
Teva Pharmaceuticals
Parsippany, NJ 07054

©2022 Teva Pharmaceuticals USA, Inc.

United States Patent Nos. 8436190, 8445524, 8609863, 8669279, 8791270, 8883836, 8895756, 9533955.
All rights reserved.

Rev. 10/2022

TRE-018

Package/Label Display Panel

Treanda® (bendamustine HCl) for Injection 25 mg/Single Use Vial

NDC 63459-390-08

Rx only

Sterile Single-Use Vial

Discard unused portion

TREANDA®

(bendamustine HCl)

for Injection

25 mg/vial

For Intravenous Infusion Only

Reconstitution and Dilution

Required (see insert)

Retain in carton until time of use

Package/Label Display Panel

Treanda® (bendamustine HCl) for Injection 100 mg/Single Use Vial, Carton Text

NDC 63459-391-20

Rx only

Sterile Single-Use Vial

Discard unused portion

TREANDA®

(bendamustine HCl)

for Injection

100 mg/vial

For Intravenous Infusion Only

Reconstitution and Dilution

Required (see insert)

Retain in carton until time of use

Package/Label Display Panel

Treanda® (bendamustine HCl) Injection 45 mg/0.5 mL Single-Dose Vial, Carton Text

Do NOT use with devices that contain polycarbonate or acrylonitrile butadiene-styrene (ABS).

NDC 63459-395-02 Rx only

Sterile Refrigerate

Treanda® (bendamustine HCl) Injection 45 mg/0.5 mL

For Intravenous Infusion Only

Further dilution is required (see insert).

Single-Dose Vial

Discard Unused Portion

Retain in carton until time of use.

Package/Label Display Panel

Treanda® (bendamustine HCl) Injection 180 mg/2 mL Single-Dose Vial, Carton Text

Do NOT use with devices that contain polycarbonate or acrylonitrile butadiene-styrene (ABS).

NDC 63459-396-02 Rx only

Sterile Refrigerate

Treanda® (bendamustine HCl) Injection 180 mg/2 mL (90 mg/mL)

For Intravenous Infusion Only

Further dilution is required (see insert).

Single-Dose Vial

Discard Unused Portion

Retain in carton until time of use.